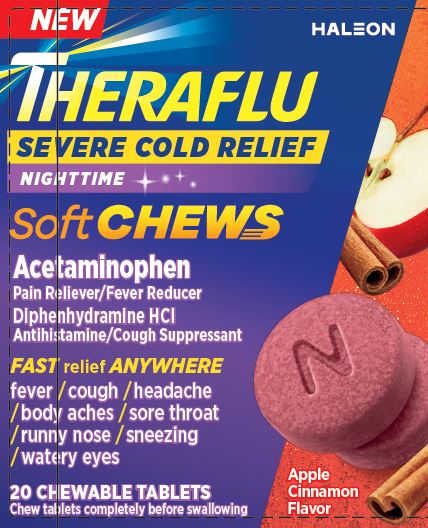 DRUG LABEL: Theraflu

NDC: 0067-0112 | Form: TABLET, CHEWABLE
Manufacturer: Haleon US Holdings LLC
Category: otc | Type: HUMAN OTC DRUG LABEL
Date: 20240905

ACTIVE INGREDIENTS: ACETAMINOPHEN 325 mg/1 1; DIPHENHYDRAMINE HYDROCHLORIDE 12.5 mg/1 1
INACTIVE INGREDIENTS: BROWN IRON OXIDE; CALCIUM GLUCONATE MONOHYDRATE; CARBOXYMETHYLCELLULOSE CALCIUM; CARNAUBA WAX; CORN SYRUP; CROSPOVIDONE, UNSPECIFIED; FD&C RED NO. 40; GLYCERIN; MANNITOL; STARCH, CORN; SODIUM GLUCONATE; SORBITOL; SORBITOL SOLUTION; SUCRALOSE; SUCROSE; COW MILK

Drug Facts

Active ingredients (in each chewable tablet)

Acetaminophen 325 mg

Diphenhydramine HCl 12.5 mg

Purposes

Pain reliever/Fever reducer

Antihistamine/Cough suppressant

Uses

- temporarily relieves these symptoms due to a cold:
  - minor aches and pains
  - sore throat pain
  - headache
  - runny nose
  - sneezing
  - itchy nose or throat
  - itchy, watery eyes due to hay fever
  - cough due to minor throat and bronchial irritation
- temporarily reduces fever

Warnings

Liver warning:This product contains acetaminophen. Severe liver damage may occur if you take

- more than 4,000 mg of acetaminophen in 24 hours
- with other drugs containing acetaminophen
- 3 or more alcoholic drinks every day while using this product

Allergy alert:Acetaminophen may cause severe skin reactions. Symptoms may include:

- skin reddening
- blisters
- rash

If a skin reaction occurs, stop use and seek medical help right away.

Sore throat warning:If sore throat is severe, persists for more than 2 days, is accompanied or followed by fever, headache, rash, nausea, or vomiting consult a doctor promptly.

Do not use

- in a child under 12 years of age
- if you are allergic to acetaminophen
- with any other drug containing acetaminophen (prescription or nonprescription). If you are not sure whether a drug contains acetaminophen, ask a doctor or pharmacist.
- with any other product containing diphenhydramine, even one used on the skin

Ask a doctor before use if you have

- liver disease
- glaucoma
- trouble urinating due to an enlarged prostate gland
- a breathing problem such as emphysema or chronic bronchitis
- cough that occurs with too much phlegm (mucus)
- cough that lasts or is chronic such as occurs with smoking, asthma or emphysema

Ask a doctor or pharmacist before use if you are

- taking sedatives or tranquilizers
- taking the blood thinning drug warfarin

When using this product

- avoid alcoholic drinks
- marked drowsiness may occur
- alcohol, sedatives and tranquilizers may increase drowsiness
- be careful when driving a motor vehicle or operating machinery
- excitability may occur, especially in children

Stop use and ask a doctor if

- fever gets worse or lasts more than 3 days
- redness or swelling is present
- new symptoms occur
- pain or cough gets worse or lasts more than 7 days
- cough comes back or occurs with rash or headache that lasts

These could be signs of a serious condition.

If pregnant or breast-feeding,

ask a health professional before use.

Keep out of reach of children.

In case of overdose, get medical help or contact a Poison Control Center right away. Prompt medical attention is critical for adults as well as for children even if you do not notice any signs or symptoms.

Directions

- do not use more than directed
- do not take more than 10 chewable tablets in 24 hours unless directed by a doctor. Take every 4 hours, while symptoms persist.

Age | Dose
adults and children 12 years of age and over | take 2 chewable tablets every 4 hours
children under 12 years of age | do not use

Other information

- each chewable tablet contains:calcium 10 mg, potassium 10 mg, sodium, 7 mg
- store at a controlled room temperature 20-25°C (68-77°F)

Inactive ingredients

brown iron oxide, calcium gluconate monohydrate, carboxymethylcellulose calcium, carnauba wax, corn syrup solids, crospovidone, FD&C red no. 40, glycerin, mannitol, natural and artificial flavors, pregelatinized starch, simethicone, sodium gluconate, sorbitol, sorbitol solution, sucralose, sucrose, whole dry milk

Questionsor comments?

call 1-855-328-5259

Generic Section

Do Not Use if seal under bottle cap imprinted with “SEALED for YOUR PROTECTION”is broken or missing.

Package/Label Principal Display Panel

NEW

THERAFLU

SEVERE COLD RELIEF

NIGHTTIME

Soft CHEWS

Acetaminophen

Pain Reliever/Fever Reducer

Diphenhydramine HCl

Antihistamine/Cough Suppressant

FASTrelief ANYWHERE

fever / cough / headache / body aches / sore throat / runny nose / sneezing / watery eyes

20 CHEWABLE TABLETS

Chew tablets completely before swallowing

Apple Cinnamon Flavor